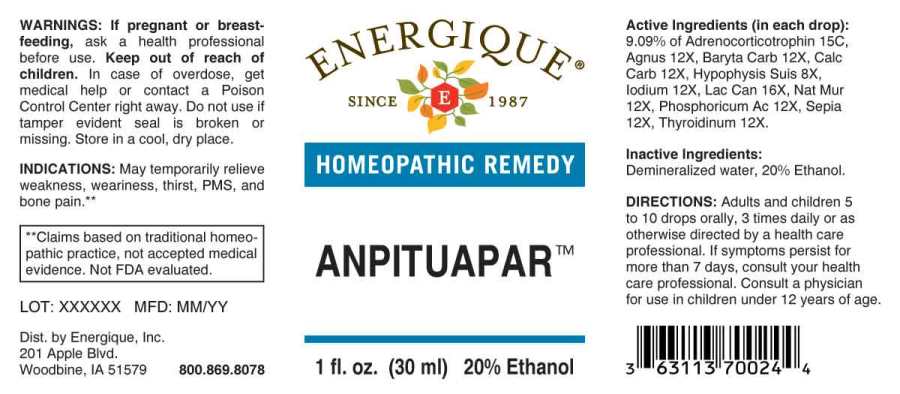 DRUG LABEL: Anpituapar
NDC: 44911-0526 | Form: LIQUID
Manufacturer: Energique, Inc.
Category: homeopathic | Type: HUMAN OTC DRUG LABEL
Date: 20230713

ACTIVE INGREDIENTS: SUS SCROFA PITUITARY GLAND 8 [hp_X]/1 mL; CHASTE TREE FRUIT 12 [hp_X]/1 mL; BARIUM CARBONATE 12 [hp_X]/1 mL; OYSTER SHELL CALCIUM CARBONATE, CRUDE 12 [hp_X]/1 mL; IODINE 12 [hp_X]/1 mL; SODIUM CHLORIDE 12 [hp_X]/1 mL; PHOSPHORIC ACID 12 [hp_X]/1 mL; SEPIA OFFICINALIS JUICE 12 [hp_X]/1 mL; THYROID 12 [hp_X]/1 mL; CANIS LUPUS FAMILIARIS MILK 16 [hp_X]/1 mL; CORTICOTROPIN 15 [hp_C]/1 mL
INACTIVE INGREDIENTS: WATER; ALCOHOL

Drug Facts:

ACTIVE INGREDIENTS:

(in each drop): 9.09% of Adrenocorticotrophin 15C, Agnus Castus 12X, Baryta Carbonica 12X, Calcarea Carbonica 12X, Hypophysis Suis 8X, Iodium 12X, Lac Caninum 16X, Natrum Muriaticum 12X, Phosphoricum Acidum 12X, Sepia 12X, Thyroidinum (Suis) 12X.

INDICATIONS:

May temporarily relieve weakness, weariness, thirst, PMS, and bone pain.**

**Claims based on traditional homeopathic practice, not accepted medical evidence. Not FDA evaluated.

WARNINGS:

If pregnant or breastfeeding, ask a health professional before use.

Keep out of reach of children. In case of overdose, get medical help or contact a Poison Control Center right away.

Do not use if tamper evident seal is broken or missing.

Store in a cool, dry place.

Keep out of reach of children. In case of overdose, get medical help or contact a Poison Control Center right away.

DIRECTIONS:

Adults and children 5 to 10 drops orally, 3 times daily or as otherwise directed by a health care professional. If symptoms persist for more than 7 days, consult your health care professional. Consult a physician for use in children under 12 years of age.

INDICATIONS:

May temporarily relieve weakness, weariness, thirst, PMS, and bone pain.**

**Claims based on traditional homeopathic practice, not accepted medical evidence. Not FDA evaluated.

INACTIVE INGREDIENTS:

Demineralized water, 20% Ethanol.

QUESTIONS:

Dist. by Energique, Inc.
201 Apple Blvd.
Woodbine, IA 51579 800.869.8078

PACKAGE LABEL DISPLAY:

ENERGIQUE
SINCE 1987
HOMEOPATHIC REMEDY
ANPITUAPAR
1 fl. oz. (30 ml)